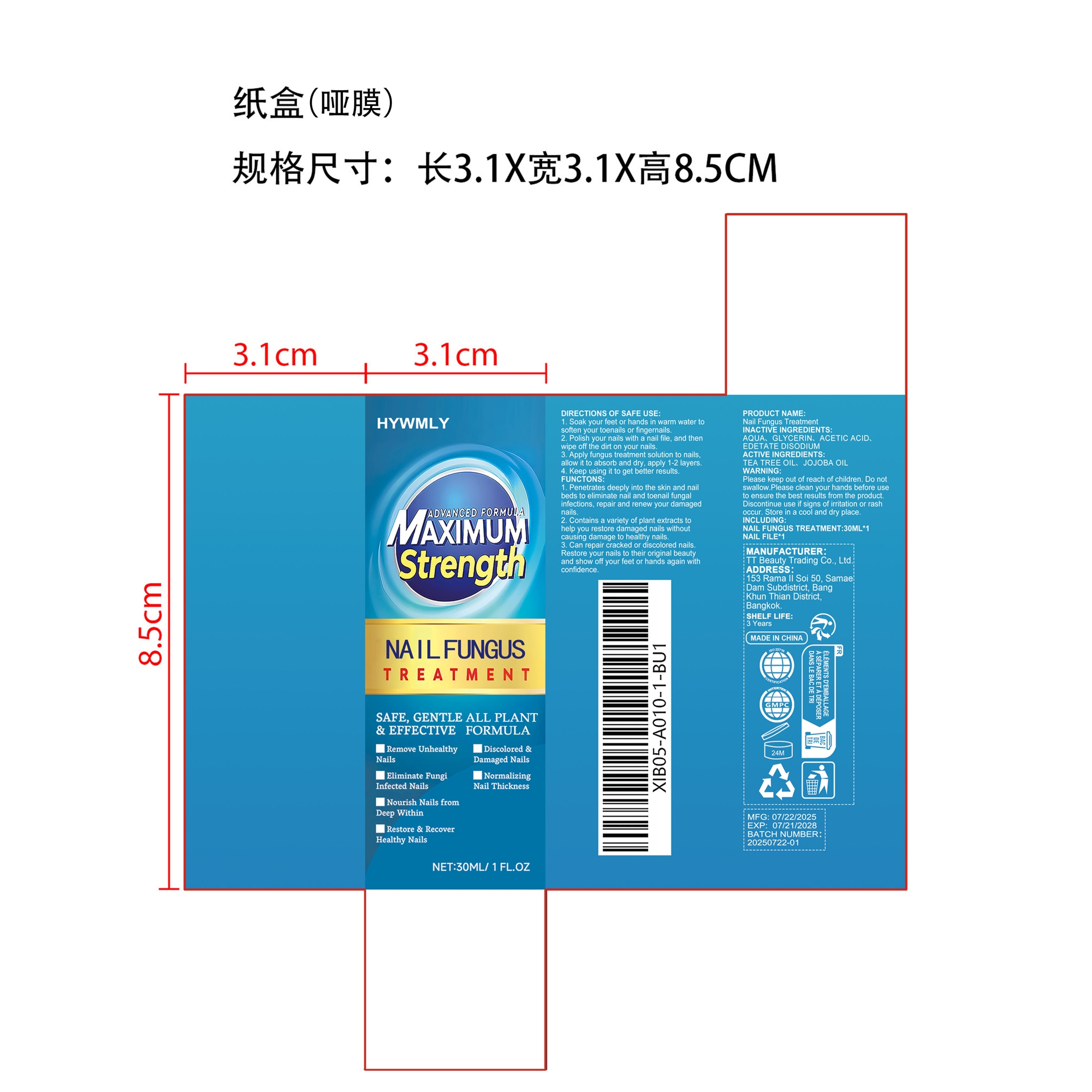 DRUG LABEL: Nail Fungus Treatment
NDC: 85206-002 | Form: LIQUID
Manufacturer: TT Beauty Trading Co., Ltd.
Category: otc | Type: HUMAN OTC DRUG LABEL
Date: 20250731

ACTIVE INGREDIENTS: TEA TREE OIL 0.03 mg/30 mg; JOJOBA OIL 0.006 mg/30 mg
INACTIVE INGREDIENTS: AQUA 26.334 mg/30 mg; GLYCERIN 3 mg/30 mg; ACETIC ACID 0.6 mg/30 mg; EDETATE DISODIUM 0.03 mg/30 mg

ACTIVE INGREDIENT

TEA TREE OIL、 JOJOBA OIL

WHEN USING

1. Soak your feet or hands in warm water to soften your toenails or fingernails.
2. Polish your nails with a nail file, and then wipe off the dirt on your nails.
3. Apply fungus treatment solution to nails, allow it to absorb and dry, apply 1-2 layers.
4. Keep using it to get better results.

PURPOSE

1. Penetrates deeply into the skin and nail beds to eliminate nail and toenail fungal infections, repair and renew your damaged nails.
2. Contains a variety of plant extracts to help you restore damaged nails without causing damage to healthy nails.
3. Can repair cracked or discolored nails. Restore your nails to their original beauty and show off your feet or hands again with confidence.

WARNINGS

Please keep out of reach of children. Do not swallow.Please clean your hands before use to ensure the best results from the product. Discontinue use if signs of irritation or rash occur. Store in a cool and dry place.

DO NOT USE

Discontinue use if signs of irritation or rash occur.

STOP USE

Discontinue use if signs of irritation or rash occur.

KEEP OUT OF REACH OF CHILDREN

Please keep out of reach of children. Do not swallow.

STORAGE AND HANDLING

Store in a cool and dry place.

INACTIVE INGREDIENT

AQUA、
GLYCERIN、
ACETIC ACID、
EDETATE DISODIUM

DOSAGE AND ADMINISTRATION

Apply fungus treatment solution to nails, allow it to absorb and dry, apply 1-2 layers.

INDICATIONS AND USAGE

Can repair cracked or discolored nails. Restore your nails to their original beauty and show off your feet or hands again with confidence.